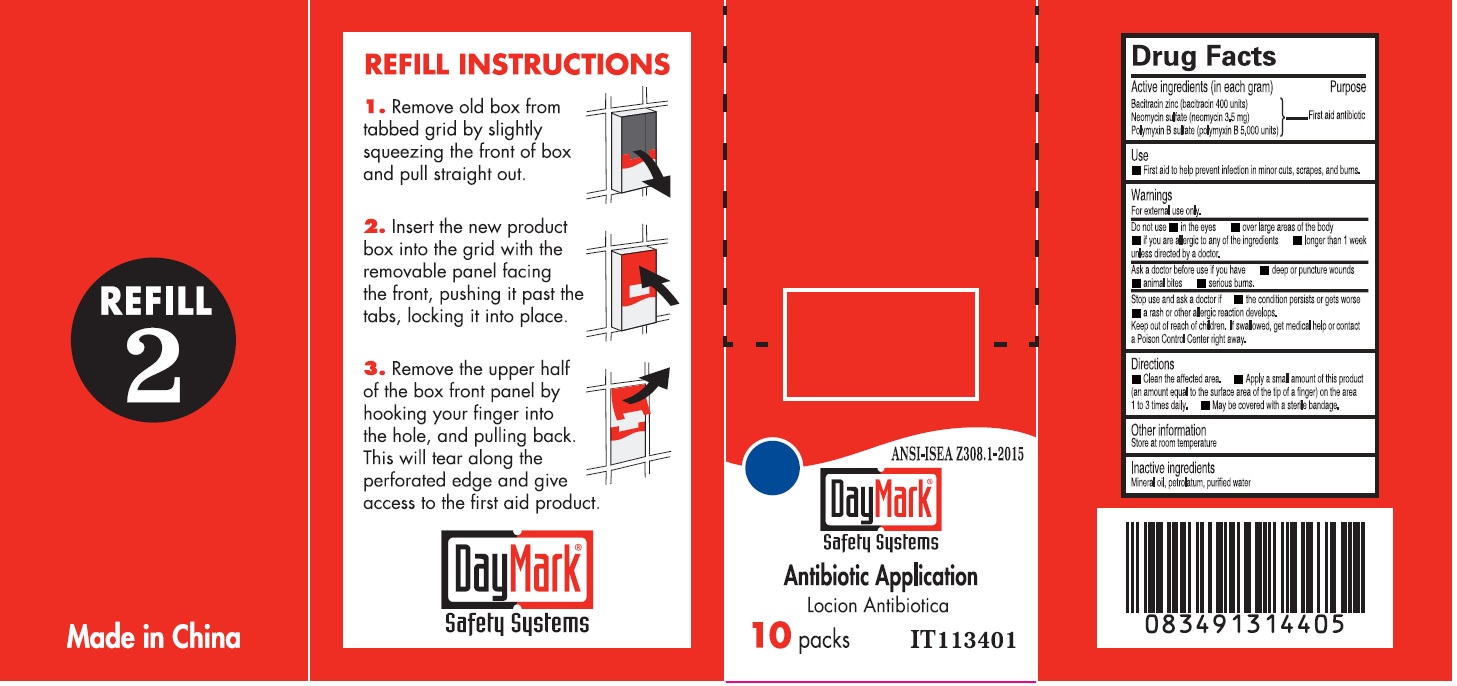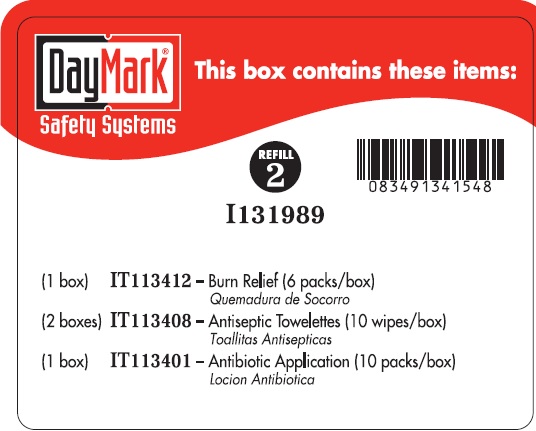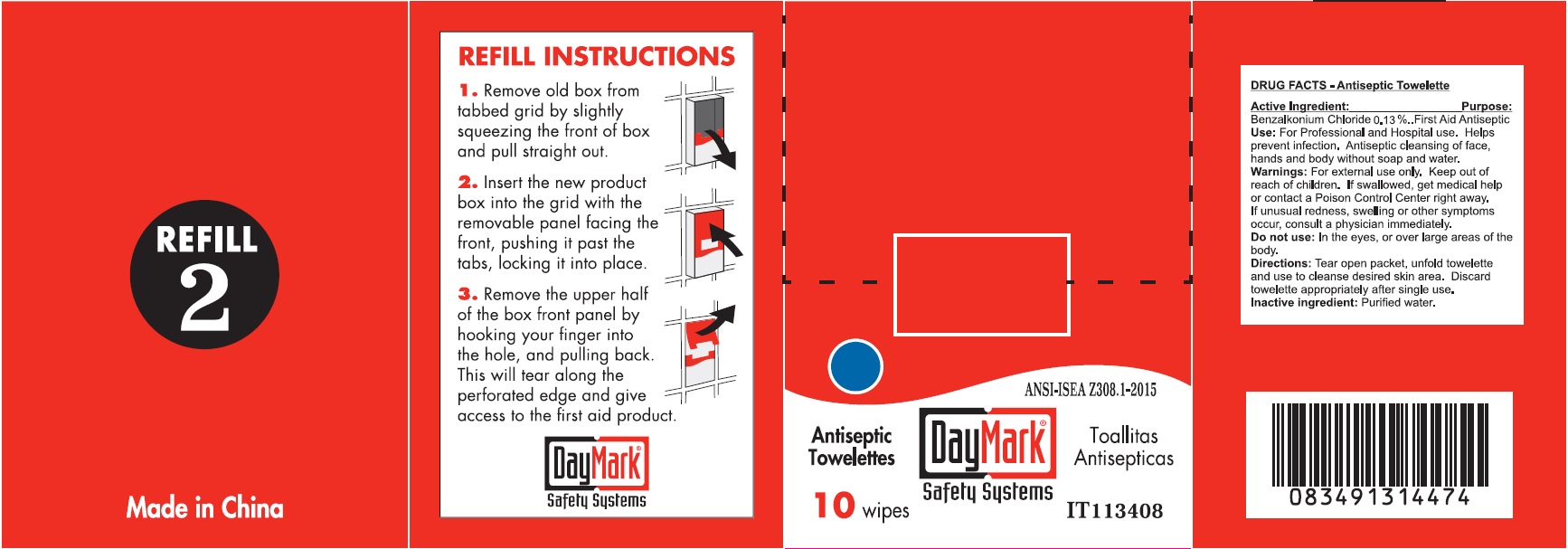 DRUG LABEL: Refill 2
NDC: 49687-0016 | Form: KIT | Route: TOPICAL
Manufacturer: CMC Group, Inc.
Category: otc | Type: HUMAN OTC DRUG LABEL
Date: 20250113

ACTIVE INGREDIENTS: BENZALKONIUM CHLORIDE 0.13 g/100 g; NEOMYCIN SULFATE 3.5 mg/1 g; POLYMYXIN B SULFATE 5000 [iU]/1 g; BACITRACIN ZINC 400 [iU]/1 g
INACTIVE INGREDIENTS: WATER; MINERAL OIL; PETROLATUM; WATER

Refill 2

Active Ingredient:

Benzalkonium Chloride 0.13%

Purpose:

First Aid Antiseptic

Use:

For Professional and Hospital use. Helps prevent infection. Antiseptic cleansing of face, hands and body without soap and water.

Warnings:

For external use only.

Keep out of reach of children.

If swallowed, get medical help or contact a Poison Control Center right away. If unusual redness, swelling or other symptoms occur, consult a physician immediately.

Do not use:

In the eyes, or over large areas of the body.

Directions:

Tear open packet, unfold towelette and use to cleanse desired skin area. Discard towelette appropriately after single use.

Inactive ingredient:

Purified water.

Active ingredients (in each gram)

Bacitracin zinc (bacitracin 400 units) Neomycin sulfate (neomycin 3.5mg) Polymyxin B sulfate (polymyxin B 5,000 units)

Purpose

First aid antibiotic

Use

- First aid to help prevent infection in minor cuts, scrapes, and burns.

Warnings

For external use only

Do not use

• in the eyes • over large areas of the body • if you are allergic to any of the ingredient • longer than 1 week unless directed by a doctor.

Ask a doctor before use if you have

• deep or punture wounds • animal bites • serious burns.

Stop use and ask a doctor if

• the condition persists or gets worse • a rash or other allergic reaction develops.

Keep out of reach of children.

If swallowed, get medical help or contact a Poison Control Center right away.

Directions

• Clean the affected area. • Apply a small amount of this product (an amount equal to the surface area of the tip of a finger) on the area 1 to 3 times daily. • May be covered with a sterile bandage.

Inactive ingredients

Mineral oil, petrolatum, purified water